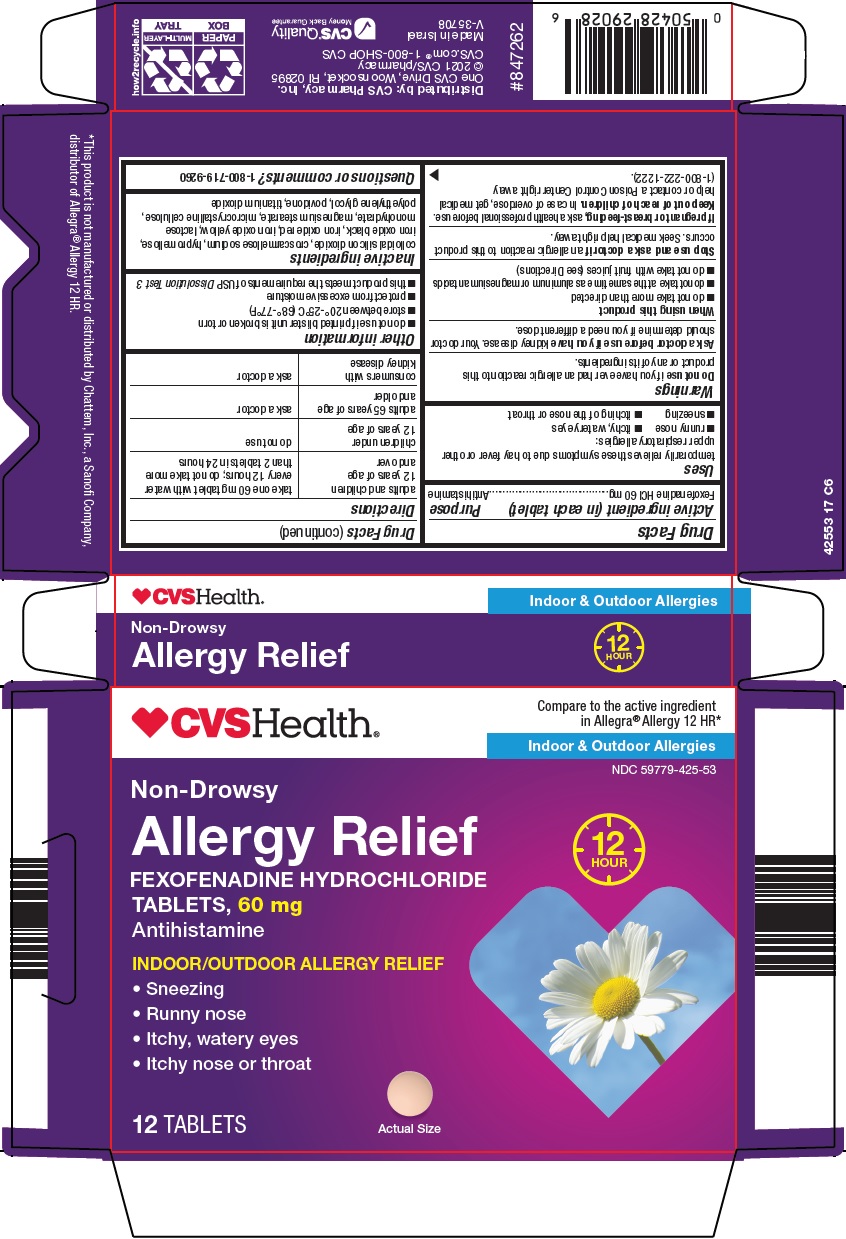 DRUG LABEL: Allergy relief
NDC: 59779-425 | Form: TABLET, FILM COATED
Manufacturer: CVS Pharmacy
Category: otc | Type: HUMAN OTC DRUG LABEL
Date: 20210916

ACTIVE INGREDIENTS: FEXOFENADINE HYDROCHLORIDE 60 mg/1 1
INACTIVE INGREDIENTS: SILICON DIOXIDE; CROSCARMELLOSE SODIUM; HYPROMELLOSE, UNSPECIFIED; FERROSOFERRIC OXIDE; FERRIC OXIDE RED; FERRIC OXIDE YELLOW; LACTOSE MONOHYDRATE; MAGNESIUM STEARATE; MICROCRYSTALLINE CELLULOSE; POLYETHYLENE GLYCOL, UNSPECIFIED; POVIDONE, UNSPECIFIED; TITANIUM DIOXIDE

CVS Pharmacy, Inc. Allergy Relief Drug Facts

Active ingredient (in each tablet)

Fexofenadine HCl 60 mg

Purpose

Antihistamine

Uses

temporarily relieves these symptoms due to hay fever or other upper respiratory allergies:

- runny nose
- itchy, watery eyes
- sneezing
- itching of the nose or throat

Warnings

Do not use

if you have ever had an allergic reaction to this product or any of its ingredients.

Ask a doctor before use if you have

kidney disease. Your doctor should determine if you need a different dose.

When using this product

- do not take more than directed
- do not take at the same time as aluminum or magnesium antacids
- do not take with fruit juices (see Directions)

Stop use and ask a doctor if

an allergic reaction to this product occurs. Seek medical help right away.

If pregnant or breast-feeding,

ask a health professional before use.

Keep out of reach of children.

In case of overdose, get medical help or contact a Poison Control Center right away (1-800-222-1222).

Directions

adults and children 12 years of age and over | take one 60 mg tablet with water every 12 hours; do not take more than 2 tablets in 24 hours
children under 12 years of age | do not use
adults 65 years of age and older | ask a doctor
consumers with kidney disease | ask a doctor

Other information

- do not use if printed blister unit is broken or torn
- store between 20°-25°C (68°-77°F)
- protect from excessive moisture
- this product meets the requirements of USP Dissolution Test 3

Inactive ingredients

colloidal silicon dioxide, croscarmellose sodium, hypromellose, iron oxide black, iron oxide red, iron oxide yellow, lactose monohydrate, magnesium stearate, microcrystalline cellulose, polyethylene glycol, povidone, titanium dioxide

Questions or comments?

1-800-719-9260

Package/Label Principal Display Panel

Compare to the active ingredient in Allegra® Allergy 12 HR

Indoor & Outdoor Allergies

Non-Drowsy

Allergy Relief

12 HOUR

FEXOFENADINE HYDROCHLORIDE TABLETS, 60 mg

Antihistamine

INDOOR/OUTDOOR ALLERGY RELIEF

-Sneezing

-Runny nose

-Itchy, watery eyes

-Itchy nose or throat

12 TABLETS

Actual Size